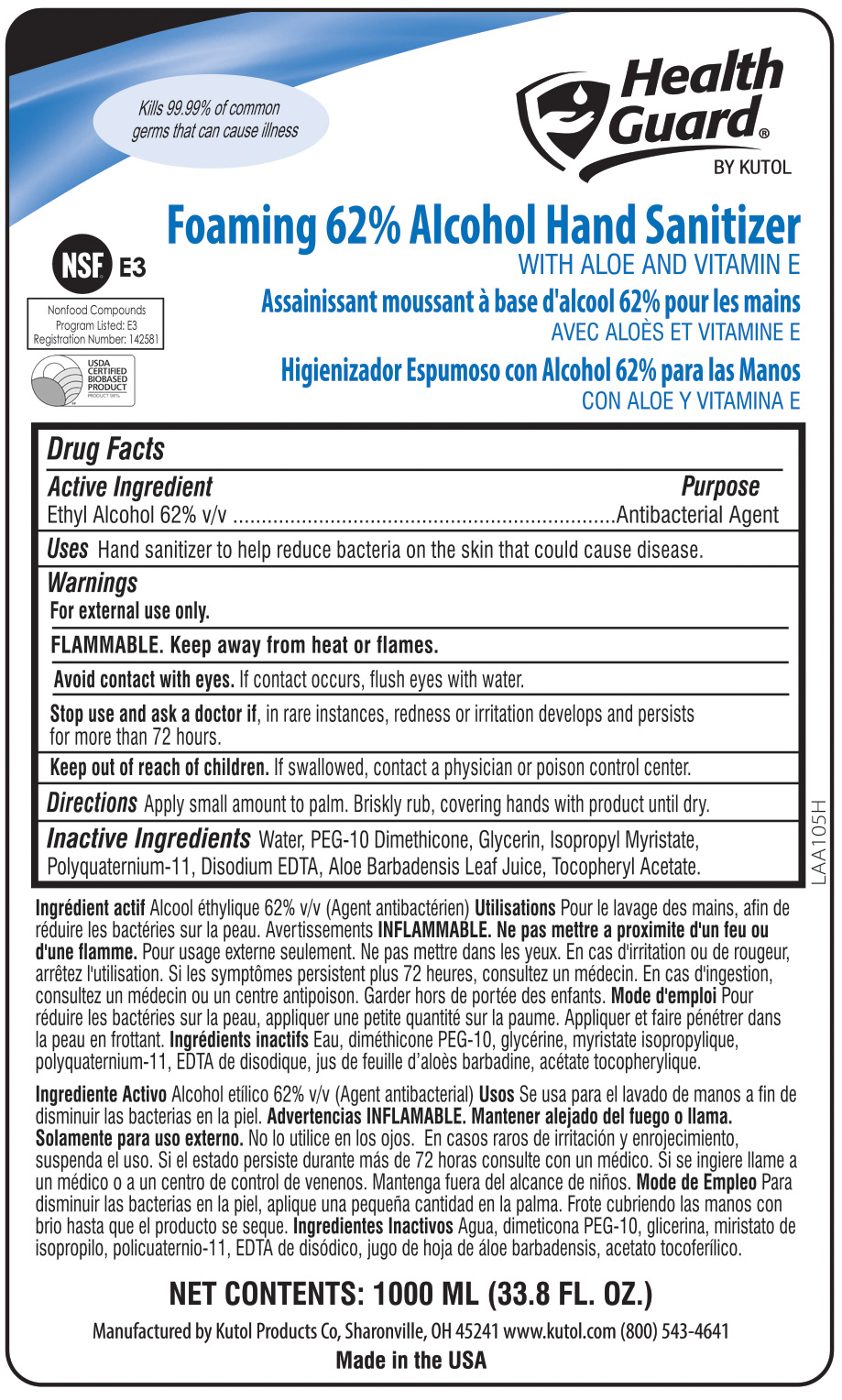 DRUG LABEL: eZFoam Foaming Alcohol Hand Sanitizer
NDC: 50865-688 | Form: SOLUTION
Manufacturer: Kutol Products Company
Category: otc | Type: HUMAN OTC DRUG LABEL
Date: 20241218

ACTIVE INGREDIENTS: ALCOHOL 62 mL/100 mL
INACTIVE INGREDIENTS: WATER; GLYCERIN; AMINOMETHYLPROPANOL (PERFLUORO-C6-C12 ETHYL)PHOSPHATE

ezFoam Foaming Alcohol Hand Sanitizer

ACTIVE INGREDIENT

Ethyl Alcohol 62% v/v.......Antibacterial Agent

INACTIVE INGREDIENT

Water, AMP-C8-18 Perfluoroalkylethyl Phosphate, Glycerin.

PURPOSE

Hand Sanitizer to help reduce bacteria on the skin that could cause disease. Recommended for repeated use.

WARNINGS

For external use only.

FLAMMABLE. Keep away from heat or flames.

Avoid contact with eyes. If eye contact occurs, flush with water.

Stop use if, in rare instances, redness or irritation develop. If condition persists for more than 72 hours, consult a physician.

Keep out of reach of children. If swallowed, contact a physician or poison control center.

DOSAGE AND ADMINISTRATION

To decrease bacteria on skin, apply small amount to palm. Briskly rub, covering hands with product until dry.

INDICATIONS AND USAGE

Hand sanitizer to help reduce bacteria on the skin that could cause disease. Recommended for repeated use.

Avoid contact with eyes. If eye contact occurs, flush with water.

Stop use if, in rare instances, redness or irritation develop. If condition persists for more than 72 hours, consult a physician.

Keep out of reach of children. If swallowed, contact a physician or poison control center.

Keep out of reach of children. If swallowed, contact a physician or poison control center.